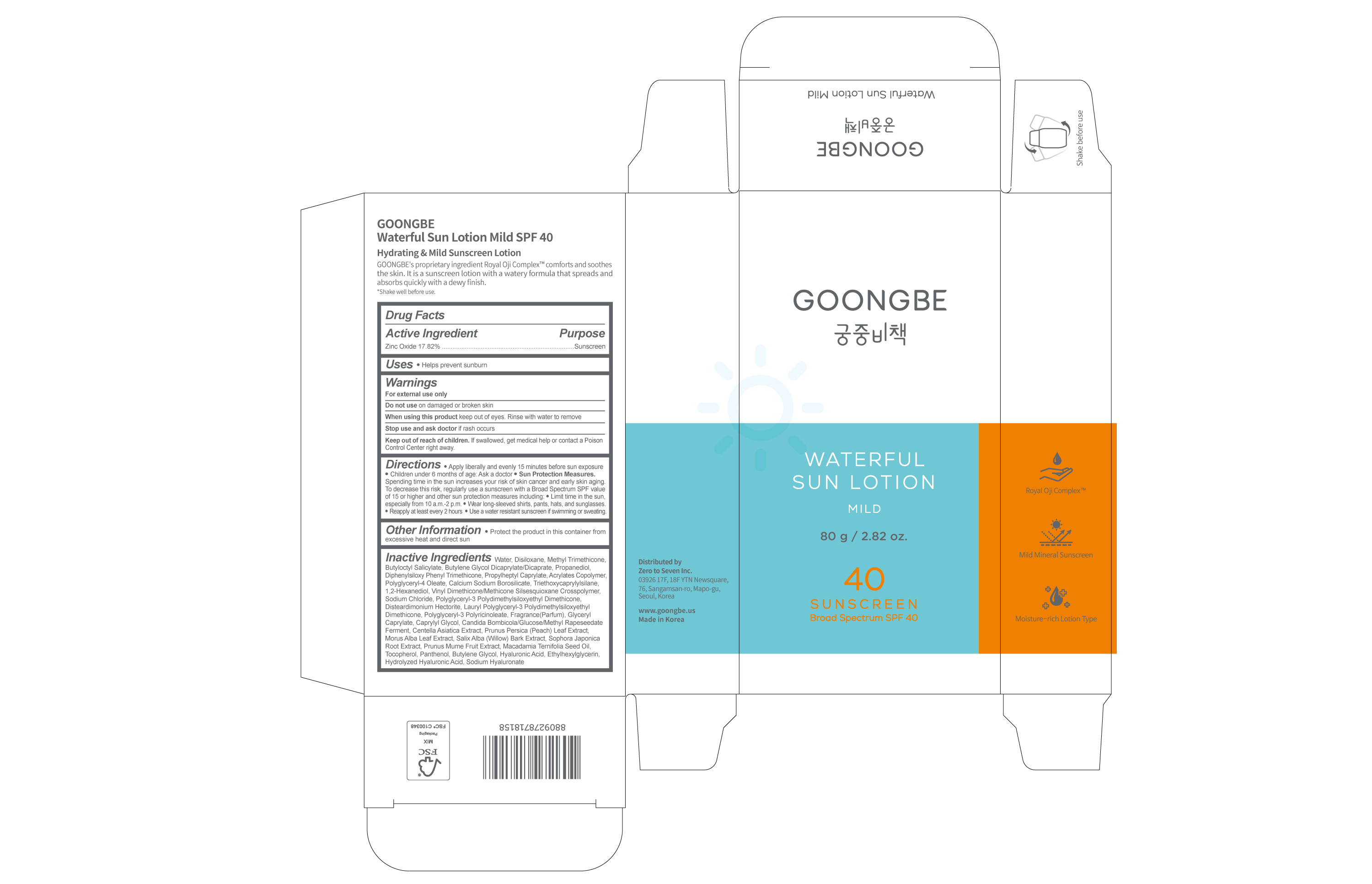 DRUG LABEL: GOONGBE Waterful SunLotion Mild SPF 40
NDC: 43319-072 | Form: LOTION
Manufacturer: Zero to Seven Inc.
Category: otc | Type: HUMAN OTC DRUG LABEL
Date: 20241118

ACTIVE INGREDIENTS: ZINC OXIDE 17.82 g/100 g
INACTIVE INGREDIENTS: BUTYLOCTYL SALICYLATE; BUTYLENE GLYCOL DICAPRYLATE/DICAPRATE; METHYL TRIMETHICONE; WATER; PROPANEDIOL

Dosage & Administration

Dosage form: Lotion

Administration: Topical

Warnings

For external use only

Do not use on damaged or broken skin.

When using this product keep out of eyes.

Rinse with water to remove Stop use and ask doctor if rash occurs

Keep out of reach of children. If swallowed, get medical help or contact a Poison Control Center right away

Inactive Ingredients

Water, Disiloxane, Methyl Trimethicone, Butyloctyl Salicylate, Butylene Glycol Dicaprylate/Dicaprate, Propanediol, Diphenylsiloxy Phenyl Trimethicone, Propylheptyl Caprylate, Acrylates Copolymer, Polyglyceryl-4 Oleate, Calcium Sodium Borosilicate, Triethoxycaprylylsilane, 1,2-Hexanediol, Vinyl Dimethicone/Methicone Silsesquioxane Crosspolymer, Sodium Chloride, Polyglyceryl-3 Polydimethylsiloxyethyl Dimethicone, Disteardimonium Hectorite, Lauryl Polyglyceryl-3 Polydimethylsiloxyethyl Dimethicone, Polyglyceryl-3 Polyricinoleate, Fragrance(Parfum), Glyceryl Caprylate, Caprylyl Glycol, Candida Bombicola/Glucose/Methyl Rapeseedate Ferment, Centella Asiatica Extract, Prunus Persica (Peach) Leaf Extract, Morus Alba Leaf Extract, Salix Alba (Willow) Bark Extract, Sophora Japonica Root Extract, Prunus Mume Fruit Extract, Macadamia Ternifolia Seed Oil, Tocopherol, Panthenol, Butylene Glycol, Hyaluronic Acid, Ethylhexylglycerin, Hydrolyzed Hyaluronic Acid, Sodium Hyaluronate

Usage

Helps prevent sunburn

Keep out of reach of children.

If swallowed, get medical help or contact a Poison Control Center right away.

Purpose

sunscreen